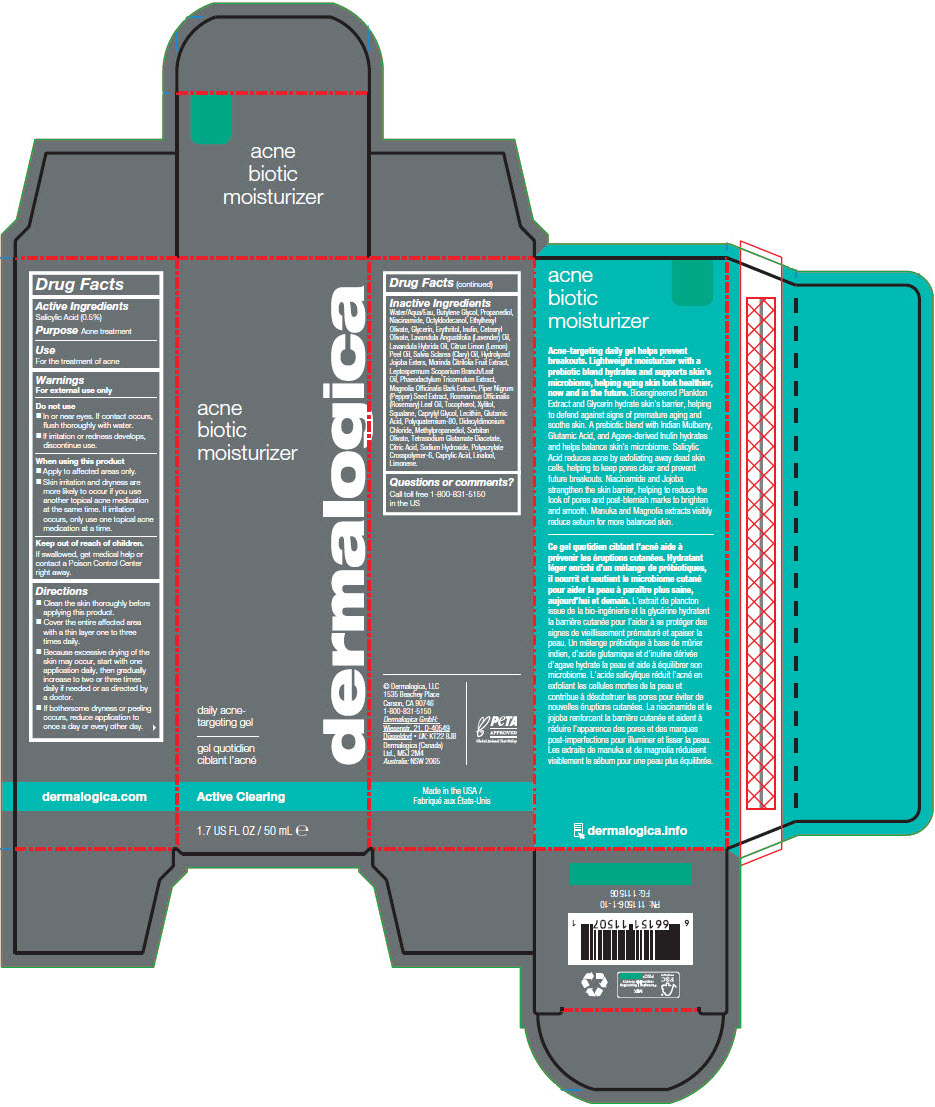 DRUG LABEL: Acne Biotic Moisturizer
NDC: 68479-350 | Form: LOTION
Manufacturer: Dermalogica, LLC.
Category: otc | Type: HUMAN OTC DRUG LABEL
Date: 20250204

ACTIVE INGREDIENTS: Salicylic Acid 0.5 mg/100 mL
INACTIVE INGREDIENTS: Water; Butylene Glycol; Propanediol; Niacinamide; Octyldodecanol; Ethylhexyl Olivate; Glycerin; Erythritol; Inulin; Cetearyl Olivate; Sorbitan Olivate; AMMONIUM ACRYLOYLDIMETHYLTAURATE, DIMETHYLACRYLAMIDE, LAURYL METHACRYLATE AND LAURETH-4 METHACRYLATE COPOLYMER, TRIMETHYLOLPROPANE TRIACRYLATE CROSSLINKED (45000 MPA.S); Glutamic Acid; POTASSIUM HYDROLYZED JOJOBA ESTERS; NONI FRUIT; Methylpropanediol; Xylitol; Caprylic Acid; Squalane; Caprylyl Glycol; Tetrasodium Glutamate Diacetate; Polyquaternium-80; MANUKA OIL; LAVENDER OIL; LAVANDIN OIL; PHAEODACTYLUM TRICORNUTUM; SOYBEAN LECITHIN; CITRIC ACID MONOHYDRATE; LEMON OIL, DISTILLED; MAGNOLIA OFFICINALIS BARK; BLACK PEPPER; ROSEMARY OIL; Didecyldimonium Chloride; CLARY SAGE OIL; Sodium Hydroxide; Tocopherol

Acne Biotic Moisturizer

Drug Facts

Active Ingredients

Salicylic Acid (0.5%)

Purpose

Acne treatment

Use

For the treatment of acne

Warnings

For external use only

Do not use

- In or near eyes. If contact occurs, flush thoroughly with water.
- If irritation or redness develops, discontinue use.

When using this product

- Apply to affected areas only.
- Skin irritation and dryness are more likely to occur if you use another topical acne medication at the same time. If irritation occurs, only use one topical acne medication at a time.

Keep out of reach of children.

If swallowed, get medical help or contact a Poison Control Center right away.

Directions

- Clean the skin thoroughly before applying this product.
- Cover the entire affected area with a thin layer one to three times daily.
- Because excessive drying of the skin may occur, start with one application daily, then gradually increase to two or three times daily if needed or as directed by a doctor.
- If bothersome dryness or peeling occurs, reduce application to once a day or every other day.

Inactive Ingredients

Water/Aqua/Eau, Butylene Glycol, Propanediol, Niacinamide, Octyldodecanol, Ethylhexyl Olivate, Glycerin, Erythritol, Inulin, Cetearyl Olivate, Lavandula Angustifolia (Lavender) Oil, Lavandula Hybrida Oil, Citrus Limon (Lemon) Peel Oil, Salvia Sclarea (Clary) Oil, Hydrolyzed Jojoba Esters, Morinda Citrifolia Fruit Extract, Leptospermum Scoparium Branch/Leaf Oil, Phaeodactylum Tricornutum Extract, Magnolia Officinalis Bark Extract, Piper Nigrum (Pepper) Seed Extract, Rosmarinus Officinalis (Rosemary) Leaf Oil, Tocopherol, Xylitol, Squalane, Caprylyl Glycol, Lecithin, Glutamic Acid, Polyquaternium-80, Didecyldimonium Chloride, Methylpropanediol, Sorbitan Olivate, Tetrasodium Glutamate Diacetate, Citric Acid, Sodium Hydroxide, Polyacrylate Crosspolymer-6, Caprylic Acid, Linalool, Limonene.

Questions or comments?

Call toll free 1-800-831-5150 in the US

PRINCIPAL DISPLAY PANEL - 50 mL Bottle Carton

acne
biotic
moisturizer

daily acne-
targeting gel

dermalogica

Active Clearing

1.7 US FL OZ / 50 mL ℮